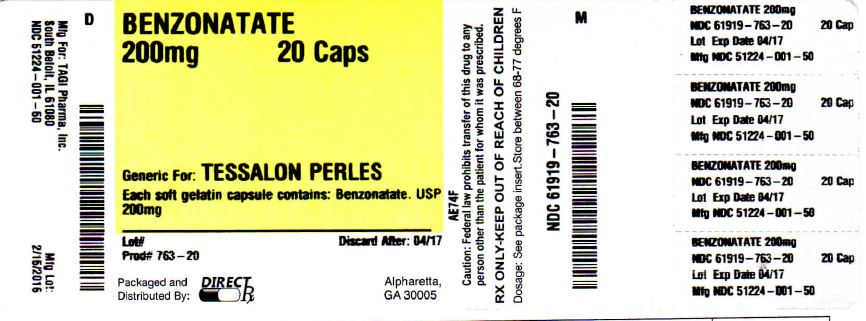 DRUG LABEL: BENZONATATE
NDC: 61919-763 | Form: CAPSULE, GELATIN COATED
Manufacturer: DIRECT RX
Category: prescription | Type: HUMAN PRESCRIPTION DRUG LABEL
Date: 20160215

ACTIVE INGREDIENTS: BENZONATATE 200 mg/1 1
INACTIVE INGREDIENTS: METHYLPARABEN; D&C YELLOW NO. 10; GELATIN; GLYCERIN; TITANIUM DIOXIDE; PROPYLPARABEN

BENZONATATE 200mg